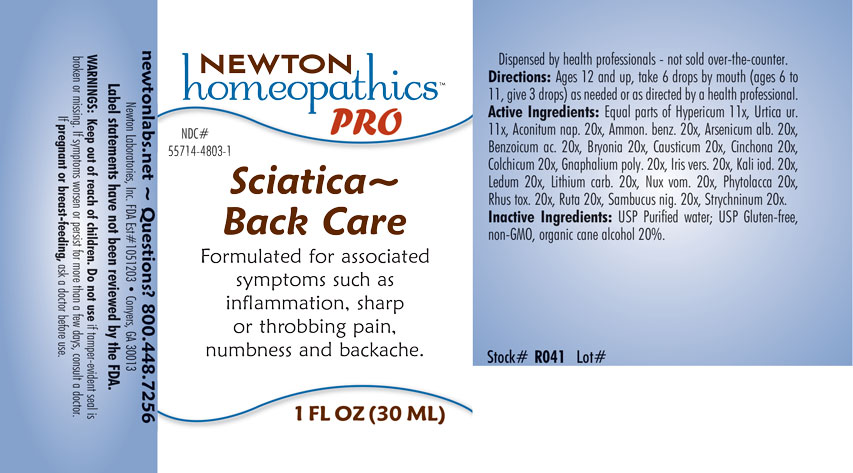 DRUG LABEL: Sciatica-Back Care
NDC: 55714-4803 | Form: LIQUID
Manufacturer: Newton Laboratories, Inc.
Category: homeopathic | Type: HUMAN OTC DRUG LABEL
Date: 20201207

ACTIVE INGREDIENTS: ACONITUM NAPELLUS 20 [hp_X]/1 mL; AMMONIUM BENZOATE 20 [hp_X]/1 mL; ARSENIC TRIOXIDE 20 [hp_X]/1 mL; BENZOIC ACID 20 [hp_X]/1 mL; BRYONIA ALBA ROOT 20 [hp_X]/1 mL; CAUSTICUM 20 [hp_X]/1 mL; CINCHONA OFFICINALIS BARK 20 [hp_X]/1 mL; COLCHICUM AUTUMNALE BULB 20 [hp_X]/1 mL; PSEUDOGNAPHALIUM OBTUSIFOLIUM 20 [hp_X]/1 mL; IRIS VERSICOLOR ROOT 20 [hp_X]/1 mL; POTASSIUM IODIDE 20 [hp_X]/1 mL; RHODODENDRON TOMENTOSUM LEAFY TWIG 20 [hp_X]/1 mL; LITHIUM CARBONATE 20 [hp_X]/1 mL; STRYCHNOS NUX-VOMICA SEED 20 [hp_X]/1 mL; PHYTOLACCA AMERICANA ROOT 20 [hp_X]/1 mL; TOXICODENDRON PUBESCENS LEAF 20 [hp_X]/1 mL; RUTA GRAVEOLENS FLOWERING TOP 20 [hp_X]/1 mL; SAMBUCUS NIGRA FLOWERING TOP 20 [hp_X]/1 mL; STRYCHNINE 20 [hp_X]/1 mL; HYPERICUM PERFORATUM 11 [hp_X]/1 mL; URTICA URENS 11 [hp_X]/1 mL
INACTIVE INGREDIENTS: WATER; ALCOHOL

Sciatica 4803L

INDICATIONS & USAGE SECTION

Formulated for associated symptoms such as inflammatoin, sharp or throbbing pain, numbness and backache.

DOSAGE & ADMINISTRATION SECTION

Directions: Ages 12 and up, take 6 drops by mouth (ages 0 to 11, give 3 drops) as needed or as directed by a health professional.

OTC - ACTIVE INGREDIENT SECTION

Equal parts of Hypericum perforatum 11x, Urtica urens 11x, Aconitum napellus 20x, Ammonium benzoicum 20x, Arsenicum album 20x, Benzoicum acidum 20x, Bryonia 20x, Causticum 20x, Cinchona officinalis 20x, Colchicum autumnale 20x, Gnaphalium polycephalum 20x, Iris versicolor 20x, Kali iodatum 20x, Ledum palustre 20x, Lithium carbonicum 20x, Nux vomica 20x, Phytolacca decandra 20x, Rhus toxicodendron 20x, Ruta graveolens 20x, Sambucus nigra 20x, Strychninum 20x.

INACTIVE INGREDIENT SECTION

Inactive Ingredients: USP Purified Water; USP Gluten-free, non-GMO, organic cane alcohol 20%.

QUESTIONS SECTION

newtonlabs.net – Questions? 800.448.7256

Newton Laboratories, Inc. FDA Est # 1051203 - Conyers, GA 30013

WARNINGS SECTION

WARNINGS: Keep out of reach of children. Do not use if tamper-evident seal is broken or missing. If symptoms worsen or persist for more than a few days, consult a doctor. If pregnant or breast-feeding, ask a doctor before use.

OTC - PREGNANCY OR BREAST FEEDING SECTION

If pregnant or breast-feeding, ask a doctor before use.

OTC - KEEP OUT OF REACH OF CHILDREN SECTION

Keep out of reach of children.